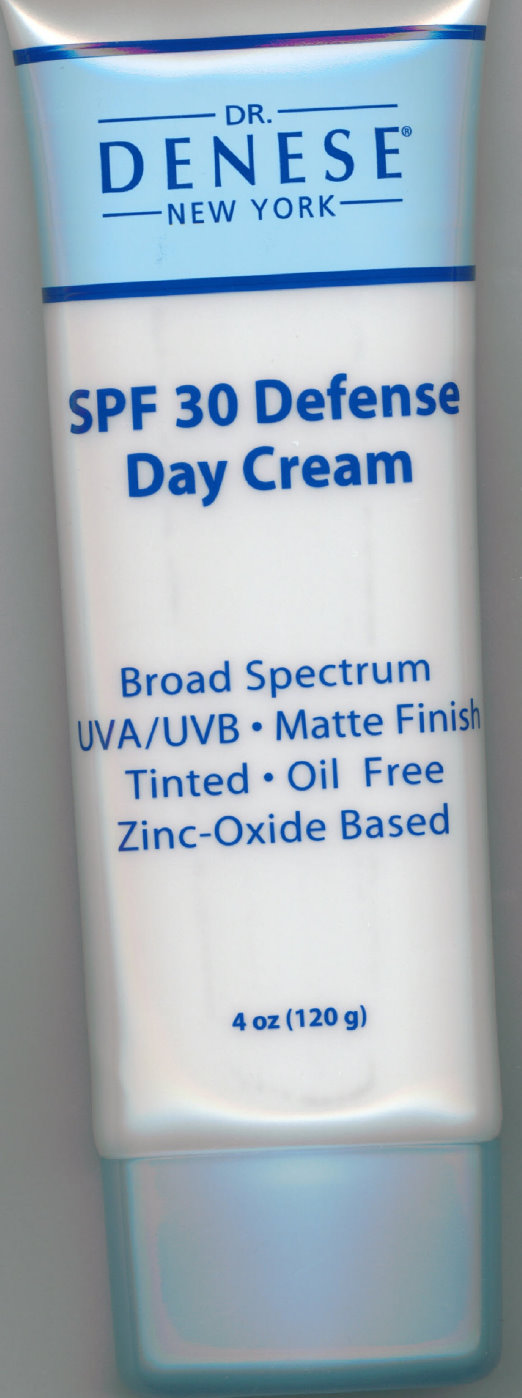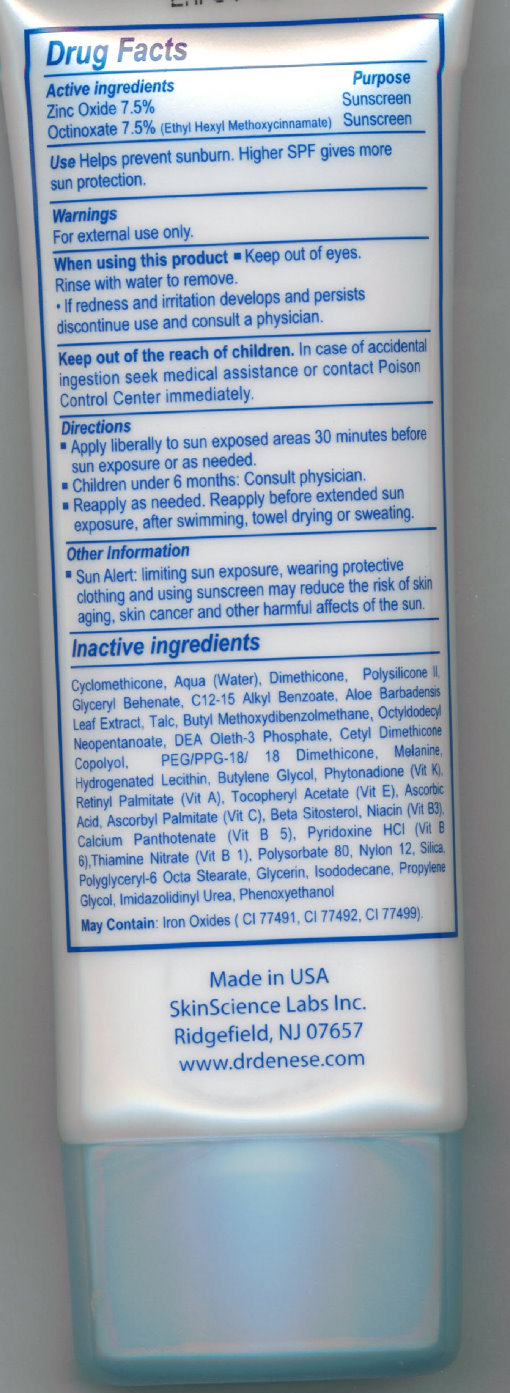 DRUG LABEL: Dr.Denese SPF 30 Defense Day
NDC: 66171-123 | Form: CREAM
Manufacturer: SkinScience Labs, Inc
Category: otc | Type: HUMAN OTC DRUG LABEL
Date: 20231212

ACTIVE INGREDIENTS: ZINC OXIDE 7.5 g/100 g; OCTINOXATE 7.5 g/100 g
INACTIVE INGREDIENTS: SILICON DIOXIDE; GLYCERIN; ISODODECANE; PROPYLENE GLYCOL; IMIDUREA; PHENOXYETHANOL; FERRIC OXIDE RED; FERRIC OXIDE YELLOW; FERROSOFERRIC OXIDE; CYCLOMETHICONE; WATER; DIMETHICONE; GLYCERYL DIBEHENATE; ALKYL (C12-15) BENZOATE; ALOE VERA LEAF; TALC; OCTYLDODECYL NEOPENTANOATE; BUTYLENE GLYCOL; PHYTONADIONE; VITAMIN A PALMITATE; ASCORBIC ACID; ASCORBYL PALMITATE; .BETA.-SITOSTEROL; NIACIN; THIAMINE MONONITRATE; POLYSORBATE 80

Dr.Denese SPF 30 Defense Day Cream

ACTIVE INGREDIENT

Active Ingredients Purpose Zinc Oxide 7.5% Sunscreen Octinoxate 7.5% (Ethyl Hexyl Methoxycinnamate) Sunscreen

PURPOSE

Uses - Helps prevent sunburn - Higher SPF provides more protection.

Use

Helps prevent sunburn. Higher SPF gives more sun protection.

Warnings For external use only

When using this product keep out of eyes. Rinse with water to remove.

STOP USE

- If redness and irritation develops and persists discontinue use and consult a physician.

Keep out of reach of children.

OTHER SAFETY INFORMATION

In case of accidental ingestion seek medical assistance or contact Poison Control Center immediately.

DOSAGE AND ADMINISTRATION

Directions - Apply liberally to sun exposed areas 30 minutes before sun exposure or as needed. - Children under 6 months : Consult physician. - Reapply as needed. Reapply before extended sun exposure, after swimming, towel drying, or sweating.

Other information - Sun alert: Limiting sun exposure, wearing protective clothing, and using sunscreen may reduce the risk of skin aging, skin cancer, and other harmful effects of the sun.

INACTIVE INGREDIENT

Inactive ingredients Cyclomethicone, Aqua (Water), Dimethicone, Polysilicone II, Glyceryl Behenate, C12-15 Alkyl Benzoate, Aloe Barbadensis Leaf Extract, Talc, Butyl Methoxydibenzolmethane, Octyldodecyl Neopentanoate, DEA Oleth-3 Phosphate, Cetyl Dimethicone Copolyol, PEG/PPG-18/18 Dimethicone, Melanine, Hydrogenated Lecithin, Butylene Glycol, Phytonadione (Vit K), Retinyl Palmitate (Vit A), Tocopheryl Acetate (Vit E), Ascorbic Acid, Ascorbyl Palmitate (Vit C), Beta Sitosterol, Niacin (Vit B3), Calcium Panthotenate (Vit B 5), Pyridoxine HCI (Vit B 6), Thiamine Nitrate (Vit B 1), Polysorbate 80, Nylon 12, Silica, Polyglyceryl-6 Octa Stearte, Glycerin, Isododecane, Propylene Glycol, Imidazolidinyl Urea, Phenoxyethanol May Contain: Iron Oxides (CI 77491, CI 77492, CI 77499).

DESCRIPTION

Made in USA SkinScience Labs Inc. Ridgefield, NJ 07657 www.drdenese.com

PACKAGE LABEL

DR. DENESE NEW YORK SPF 30 Defense Day Cream Broad Spectrum UVA/UVB - Matte Finish Tinted - Oil Free Zinc-Oxide Based 4 oz (120 g)

PACKAGE LABEL

Drug Facts Made in USA SkinScience Labs Inc. Ridgefield, NJ 07657 www.drdenese.com